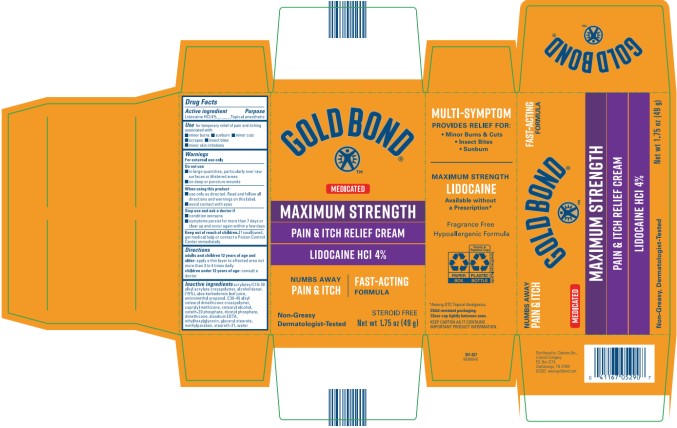 DRUG LABEL: Gold Bond Medicated Pain and Itch Relief
NDC: 41167-0529 | Form: CREAM
Manufacturer: Chattem, Inc.
Category: otc | Type: HUMAN OTC DRUG LABEL
Date: 20260114

ACTIVE INGREDIENTS: LIDOCAINE HYDROCHLORIDE 4 g/100 g
INACTIVE INGREDIENTS: ALCOHOL; ALOE VERA LEAF; AMINOMETHYLPROPANOL; C30-45 ALKYL CETEARYL DIMETHICONE CROSSPOLYMER; CAPRYLYL TRISILOXANE; CETOSTEARYL ALCOHOL; CETETH-20 PHOSPHATE; DIHEXADECYL PHOSPHATE; DIMETHICONE; EDETATE DISODIUM; ETHYLHEXYLGLYCERIN; GLYCERYL MONOSTEARATE; METHYLPARABEN; STEARETH-21; WATER; CARBOMER INTERPOLYMER TYPE A (55000 CPS)

Gold Bond Medicated Pain and Itch Relief - Reformulated

Gold Bond® Medicated

Pain & Itch Relief Cream with Lidocaine

Drug Facts

Purpose

Lidocaine HCl 4%.............................................................................................................................Topical anesthetic

Use

for temporary relief of pain and itching associated with:

■ minor burns ■ sunburn ■ minor cuts ■ scrapes ■ insect bites ■ minor skin irritations

Warnings

For external use only

Do not use

■ in large quantities, particularly over raw surfaces or blistered areas ■ on deep or puncture wounds

When using this product

■ use only as directed. Read and follow all directions and warnings on this label.

■ avoid contact with eyes

Stop use and ask a doctor if

■ condition worsens

■ symptoms persist for more than 7 days or clear up and occur again within a few days

Keep out of reach of children.

If swallowed, get medical help or contact a Poison Control Center immediately.

Directions

adults and children 12 years of age and older: apply a thin layer to affected area not more than 3 to 4 times daily

children under 12 years of age: consult a doctor

Inactive ingredients:

acrylates/C10-30 alkyl acrylate crosspolymer, alcohol denat. (15%), aloe barbadensis leaf juice, aminomethyl propanol, C30-45 alkyl cetearyl dimethicone crosspolymer, caprylyl methicone, cetearyl alcohol, ceteth-20 phosphate, dicetyl phosphate, dimethicone, disodium EDTA, ethylhexylglycerin, glyceryl stearate, methylparaben, steareth-21, water

Close cap tightly between uses.

PRINCIPAL DISPLAY PANEL

GOLD BOND
Maximum Strength
Pain and Itch Relief Cream
Net wt.1.75 oz (49 g)